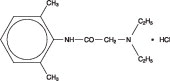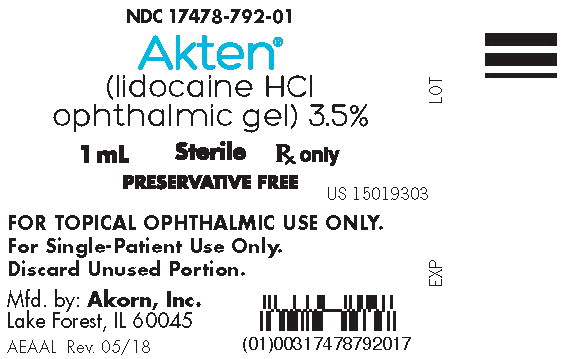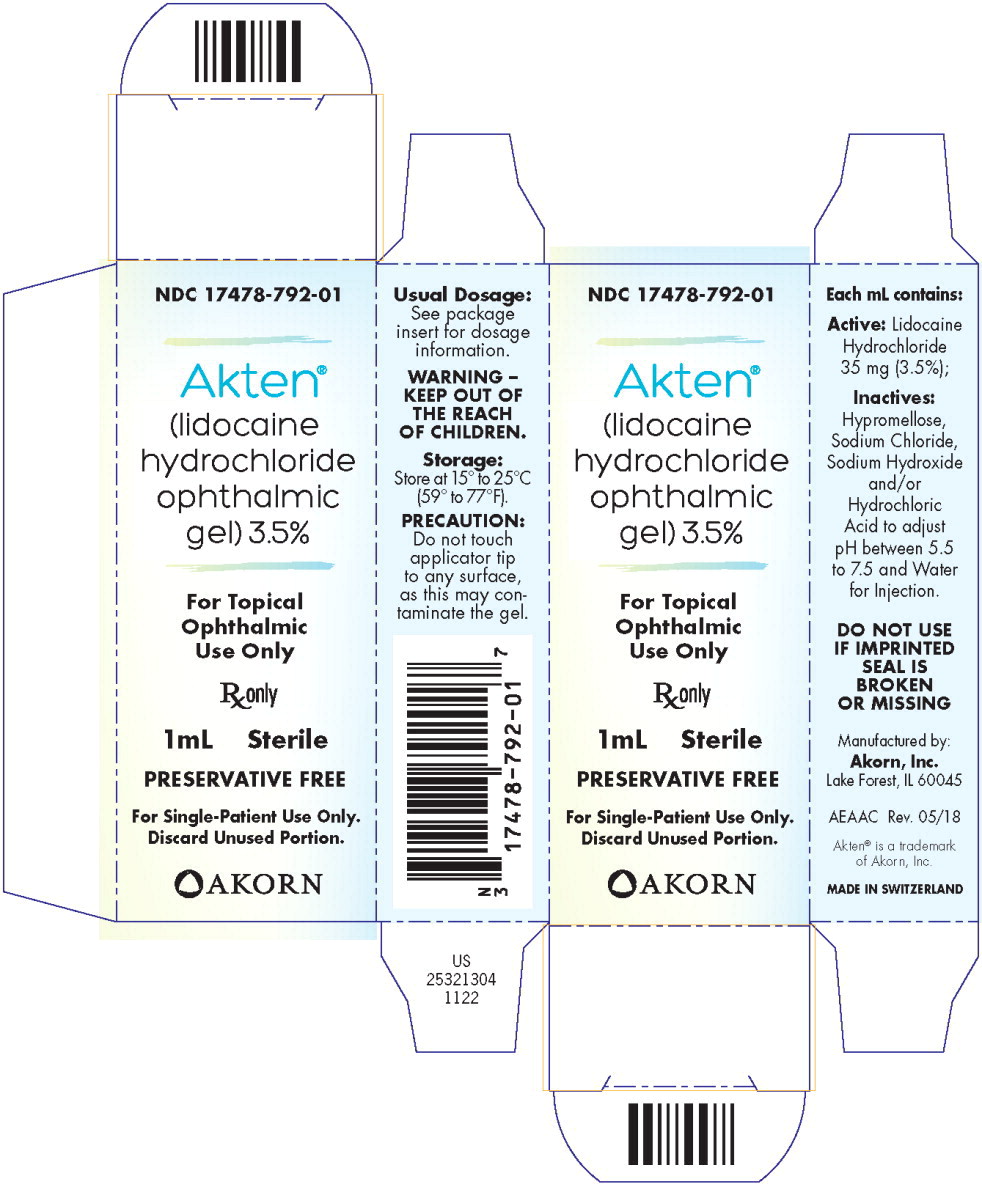 DRUG LABEL: Akten
NDC: 17478-792 | Form: GEL
Manufacturer: Akorn
Category: prescription | Type: HUMAN PRESCRIPTION DRUG LABEL
Date: 20211115

ACTIVE INGREDIENTS: Lidocaine Hydrochloride Anhydrous 35 mg/1 mL
INACTIVE INGREDIENTS: Hypromelloses; Sodium Chloride; Sodium Hydroxide; Hydrochloric Acid; Water

HIGHLIGHTS OF PRESCRIBING INFORMATION

These highlights do not include all the information needed to use AKTEN® safely and effectively. See full prescribing information for AKTEN®.
AKTEN® (lidocaine hydrochloride ophthalmic gel), for topical ophthalmic use
Initial U.S. Approval: 1972

RECENT MAJOR CHANGES

Warnings and Precautions (5.3) | 2/2022

1 INDICATIONS AND USAGE

AKTEN® is a local anesthetic indicated for ocular surface anesthesia during ophthalmologic procedures. (1)

2 DOSAGE AND ADMINISTRATION

The recommended dose of AKTEN® is 2 drops applied to the ocular surface in the area of the planned procedure. Additional anesthesia may be reapplied as needed. (2)

3 DOSAGE FORMS AND STRENGTHS

AKTEN® 3.5% (35 mg/mL) Ophthalmic Gel. (3)

4 CONTRAINDICATIONS

None. (4)

5 WARNINGS AND PRECAUTIONS

- For Topical Ophthalmic Use: Not for Injection. (5.1)
- Corneal Opacification: Prolonged use of a topical ocular anesthetic may produce permanent corneal opacification and ulceration with accompanying visual loss. (5.2)
- For Administration by Healthcare Provider: AKTEN® is not intended for patient self-administration. (5.3)

6 ADVERSE REACTIONS

Most common adverse reactions are conjunctival hyperemia, corneal epithelial changes, headache, and burning upon instillation. (6)

To report SUSPECTED ADVERSE REACTIONS, contact Akorn Operating Company LLC at 1-800-932-5676 or FDA at 1-800-FDA-1088 or www.fda.gov/medwatch.

FULL PRESCRIBING INFORMATION

1 INDICATIONS AND USAGE

AKTEN® is indicated for ocular surface anesthesia during ophthalmologic procedures.

2 DOSAGE AND ADMINISTRATION

The recommended dose of AKTEN® is 2 drops applied to the ocular surface in the area of the planned procedure. AKTEN® may be reapplied to maintain anesthetic effect.

3 DOSAGE FORMS AND STRENGTHS

AKTEN® Ophthalmic Gel, 3.5% contains 35 mg per mL of lidocaine hydrochloride for topical ophthalmic administration.

4 CONTRAINDICATIONS

None.

5 WARNINGS AND PRECAUTIONS

5.1 For Topical Ophthalmic Use

AKTEN® is indicated for topical ophthalmic use. Not for Injection.

5.2 Corneal Opacification

Prolonged use of a topical ocular anesthetic may produce permanent corneal opacification and ulceration with accompanying visual loss.

5.3 For Administration by Healthcare Provider

AKTEN® is indicated for administration under the direct supervision of a healthcare provider. AKTEN® is not intended for patient self-administration.

6 ADVERSE REACTIONS

Most common adverse reactions are conjunctival hyperemia, corneal epithelial changes, headache, and burning upon instillation.

8 USE IN SPECIFIC POPULATIONS

8.1 Pregnancy

Reproduction studies for lidocaine have been performed in both rats and rabbits. There was no evidence of harm to the fetus at subcutaneous doses up to 50 mg/kg lidocaine (more than 800 fold greater than the human dose on a body weight basis) in the rat model. There are, however, no adequate and well controlled studies in pregnant women. Because animal reproduction studies are not always predictive of human response, this drug should be used in pregnancy only if clearly needed.

8.3 Nursing Mothers

Lidocaine is secreted in human milk. The clinical significance of this observation is unknown. Although no systemic exposure is expected with administration of AKTEN®, caution should be exercised when AKTEN® is administered to a nursing woman.

8.4 Pediatric Use

Safety and efficacy in pediatric patients have been extrapolated from studies in older subjects and studies in pediatric patients using different formulations of lidocaine.

8.5 Geriatric Use

No overall clinical differences in safety or effectiveness were observed between the elderly and other adult patients.

10 OVERDOSAGE

Prolonged use of a topical ocular anesthetic may produce permanent corneal opacification and ulceration with accompanying visual loss.

Acute emergencies from local anesthetics are generally related to high plasma levels encountered during therapeutic use of local anesthetics or to unintended subarachnoid injection of local anesthetic solution.

However, topical ocular application of AKTEN® is not expected to result in systemic exposure.

11 DESCRIPTION

AKTEN® (lidocaine hydrochloride ophthalmic gel) 3.5% is a sterile, preservative-free, single-patient use ophthalmic gel preparation for topical ocular anesthesia. Lidocaine hydrochloride is designated chemically as acetamide, 2-(diethylamino)-N-(2,6-dimethylphenyl) monohydrochloride with a molecular formula of C14H22N2O • HCl and molecular weight of 270.8. The structural formula of the active ingredient is:

AKTEN® contains 35 mg of lidocaine hydrochloride per mL as the active ingredient. AKTEN® also contains Hypromellose, Sodium Chloride, and Water for Injection as inactive ingredients in the 1 mL tube configuration. AKTEN® contains Hypromellose, Sodium Chloride, and Water for Injection as inactive ingredients in the 5 mL in 10 mL bottle configuration. The pH may be adjusted to 5.5 to 7.5 with Hydrochloric Acid and/or Sodium Hydroxide.

12 CLINICAL PHARMACOLOGY

12.1 Mechanism of Action

AKTEN® is a local anesthetic agent that stabilizes the neuronal membrane by inhibiting the ionic fluxes required for the initiation and conduction of impulses, thereby effecting local anesthetic action. Anesthesia generally occurs between 20 seconds to 1 minute and persists for 5 to 30 minutes.

12.3 Pharmacokinetics

Lidocaine may be absorbed following topical administration to mucous membranes. Its rate and extent of absorption depend upon various factors such as concentration, the specific site of application, viscosity of the agent, and duration of exposure.

The plasma binding of lidocaine is dependent on drug concentration, and the fraction bound decreases with increasing concentration. At concentrations of 1 to 4 mcg of free base per mL, 60 to 80 percent of lidocaine is protein bound. Binding is also dependent on the plasma concentration of the alpha-1-acid glycoprotein.

Lidocaine is metabolized rapidly by the liver, and metabolites and unchanged drug are excreted by the kidneys. Biotransformation includes oxidative N-dealkylation, ring hydroxylation, cleavage of the amide linkage, and conjugation. N-dealkylation, a major pathway of biotransformation, yields the metabolites monoethylglycinexylidide and glycinexylidide. The pharmacologic/toxicologic actions of these metabolites are similar to, but less potent than, those of lidocaine. Approximately 90% of lidocaine administered is excreted in the form of various metabolites, and less than 10% is excreted unchanged. The primary metabolite in urine is a conjugate of 4-hydroxy-2, 6-dimethylaniline.

Studies of lidocaine metabolism following intravenous bolus injections have shown that the elimination half-life of this agent is typically 1.5 to 2 hours. Because of the rate at which lidocaine is metabolized, any condition that affects liver function may alter lidocaine kinetics. The half-life may be prolonged twofold or more in patients with liver dysfunction. Renal dysfunction does not affect lidocaine kinetics but may increase the accumulation of metabolites.

13 NONCLINICAL TOXICOLOGY

13.1 Carcinogenesis, Mutagenesis, Impairment of Fertility

Long-term studies in animals have not been performed to evaluate the carcinogenic potential of AKTEN®.

14 CLINICAL STUDIES

The effect of AKTEN® on ocular anesthesia was studied in a multi-center, randomized, controlled, double-blind study.

A total of 209 subjects were enrolled, with 54, 51, 53, and 51 subjects randomized to the sham, AKTEN® 1.5%, AKTEN® 2.5%, and AKTEN® 3.5% groups, respectively. Ocular anesthesia was achieved within 5 minutes of anesthetic application by 47 of 51 subjects (92%) in the AKTEN® 3.5% group.

The mean time to anesthesia onset ranged from 20 seconds to 5 minutes and was not affected by AKTEN® dose. The mean time to anesthesia onset was approximately 60 seconds, with a median onset time of 40 seconds for the AKTEN® 3.5% group. Among the subjects in the AKTEN® groups who achieved anesthesia within 5 minutes, approximately 90% had achieved anesthesia within 60 seconds of application.

The duration of anesthesia generally ranged from approximately 5 minutes to 30 minutes, with mean anesthesia durations of approximately 15 minutes for the AKTEN® 3.5% group.

Approximately 84% of the subjects in the AKTEN® 3.5% group experienced anesthesia for at least 5 minutes, approximately 55% of subjects experienced anesthesia for 10 minutes or longer and 27% experienced anesthesia for 15 minutes or longer. The anesthetic effect of additional applications of AKTEN® has not been evaluated.

16 HOW SUPPLIED/STORAGE AND HANDLING

AKTEN® (lidocaine hydrochloride ophthalmic gel) 3.5% is supplied as a clear gel for single-patient use as follows:

NDC 17478-792-01 | 1 mL fill in a white polyfoil tube*
NDC 17478-792-25 | Package of 25 units of 1 mL fill in a white polyfoil tube* (NDC 17478-792-01)
NDC 17478-792-10 | 5 mL fill in a 10 mL natural, round plastic dropper bottle

Storage

Store at 15°C to 25°C (59°F to 77°F).

Keep container closed and protected from light in the original carton until use. Discard after use.

AKORN

Manufactured by: Akorn Operating Company LLC
Lake Forest, IL 60045
*Made in Switzerland
Patent Pending
AE00N Revised 2/2022

Principal Display Panel Text for Container Label:

NDC 17478-792-01

Akten®

(lidocaine HCl

ophthalmic gel) 3.5%

1 mL Sterile Rx only

PRESERVATIVE FREE

Principal Display Panel Text for Carton Label:

NDC 17478-792-01

Akten®

(lidocaine

hydrochloride

ophthalmic

gel) 3.5%

For Topical

Ophthalmic

Use Only

Rx only

1 mL Sterile

PRESERVATIVE FREE

For Single-Patient Use Only.

Discard Unused Portion.

Akorn Logo